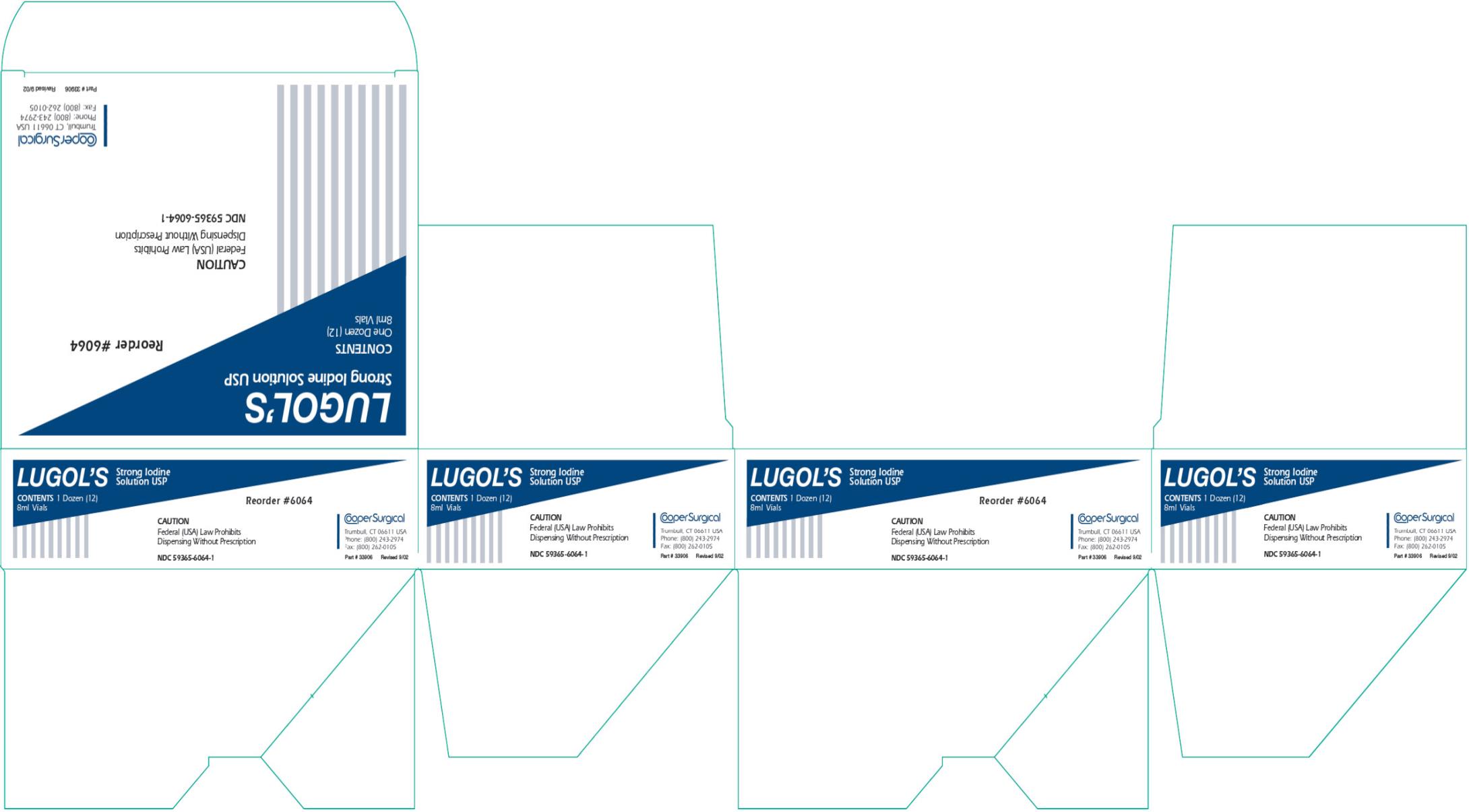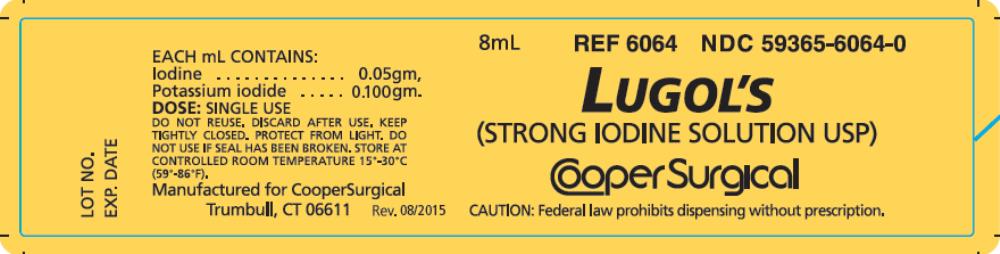 DRUG LABEL: Lugols Strong Iodine
NDC: 59365-6064 | Form: SOLUTION
Manufacturer: CooperSurgical, Inc.
Category: prescription | Type: HUMAN PRESCRIPTION DRUG LABEL
Date: 20160525

ACTIVE INGREDIENTS: IODINE 0.05 g/1 mL; POTASSIUM IODIDE 0.100 g/1 mL

Lugols Strong Iodine Solution

CONTENTS

Iodine 0.05 g/ml, Potassium Iodide 0.100 g/ml.

DESCRIPTION

LUGOL’S is an aqueous solution containing Iodine 5%, and potassium iodide 10%, w/v (LUGOL’s Solution). LUGOL’s is a transparent liquid with a deep brown color and the odor of iodine.

HOW SUPPLIED

LUGOL’S is supplied in 8 ml glass single-use bottles.

INDICATIONS AND USAGE

LUGOL’s is a topical antiseptic. Strong Iodine Solution is a germicide and fungicide. LUGOL’s is preservative-free.

ADMINISTRATION

LUGOL’S is applied directly to areas needing antiseptic.

WARNINGS

For External Use Only.

CONTRAINDICATIONS

Iodide preparations are contraindicated in patients with known sensitivity to the drugs.

CAUTION

Federal law restricts this device to sale by or on the order of a physician.

STORAGE

Keep tightly closed. Protect from light. DO NOT use if seal has been broken. Store at controlled room temperature 15°-30°C (59°-86°F).

DISPOSAL

Opened containers with unused portions of product and applicator swabs containing residual product should be placed in a suitable, dry container for disposal following local hazardous waste practices. Waste containing LUGOL’S should not be subjected to any thermal process whether intended for destruction or recycling purposes.

PRINCIPAL DISPLAY PANEL

Lugol’s
Strong Iodine Solution USP
Contents
One Dozen (12)
8ml Vials

PRINCIPAL DISPLAY PANEL

8mL NDC 59365-6064-0
Lugol’s
(STRONG IODINE SOLUTIONS USP)